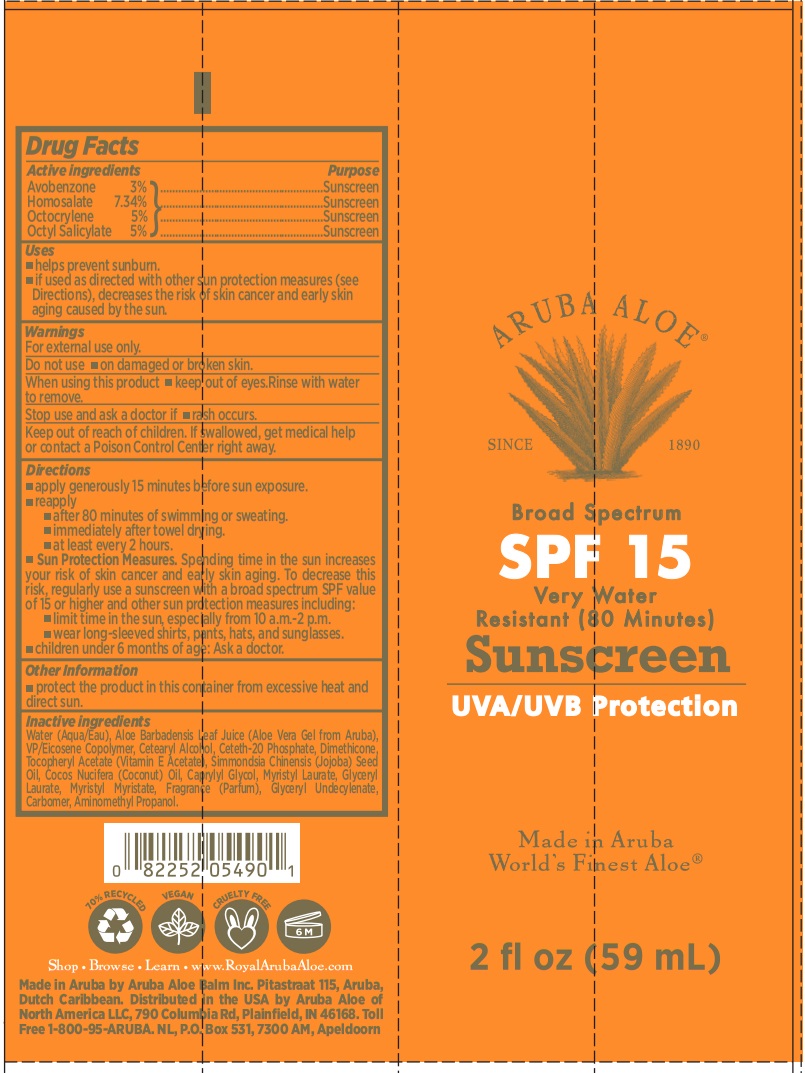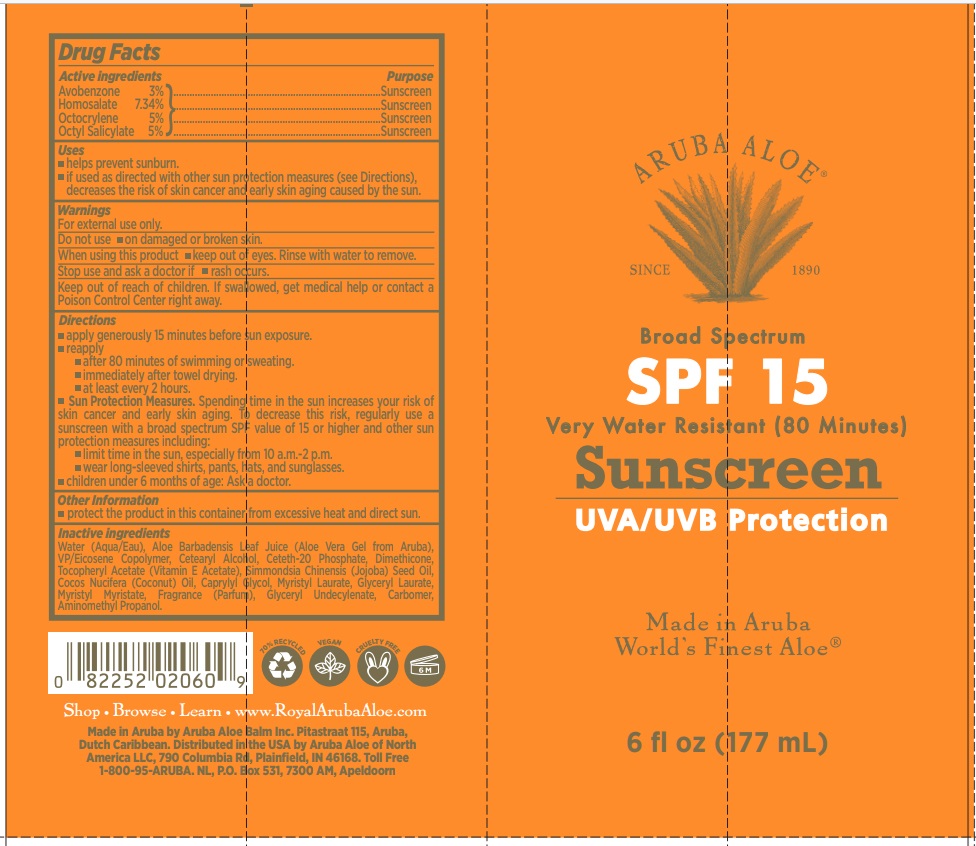 DRUG LABEL: Broad Spectrum SPF15 Very Water Resistant (80 Minutes) Sunscreen
NDC: 53675-206 | Form: CREAM
Manufacturer: Aruba Aloe Balm NV
Category: otc | Type: HUMAN OTC DRUG LABEL
Date: 20260211

ACTIVE INGREDIENTS: AVOBENZONE 30 mg/1 mL; HOMOSALATE 73.4 mg/1 mL; OCTOCRYLENE 50 mg/1 mL; OCTISALATE 50 mg/1 mL
INACTIVE INGREDIENTS: WATER; ALOE VERA LEAF; CETOSTEARYL ALCOHOL; CETETH-20 PHOSPHATE; DIMETHICONE; .ALPHA.-TOCOPHEROL ACETATE; JOJOBA OIL; COCONUT OIL; CAPRYLYL GLYCOL; GLYCERYL LAURATE; MYRISTYL MYRISTATE; CARBOMER HOMOPOLYMER, UNSPECIFIED TYPE; AMINOMETHYLPROPANOL

Broad Spectrum SPF15 Very Water Resistant (80 minutes) Sunscreen

Active ingredients

Avobenzone 3%
Homosalate 7.34%
Octocrylene 5%
Octyl Salicylate 5%

Purpose

Sunscreen

Uses

- helps prevent sunburn.
- if used as directed with other sun protection measures (see Directions), decreases the risk of skin cancer and early skin aging caused by the sun.

Warnings

For external use only.

Do not use

- on damaged or broken skin.

When using this product

- keep out of eyes.Rinse with water to remove

Stop use and ask a doctor if

- rash occurs

Keep out of reach of children.

- If swallowed, get medical help or contact a Poison Control Center right away

Directions

- apply generously 15 minutes before sun exposure.
- reapply
- after 80 minutes of swimming or sweating.
- immediately after towel drying.
- at least every 2 hours.
- Sun Protection Measures.Spending time in the sun increases your risk of skin cancer and early skin aging. To decrease this risk, regularly use a sunscreen with a broad spectrum SPF value of 15 or higher and other sun protection measures including:
- limit time in the sun, especially from 10 a.m.-2 p.m.
- wear long-sleeved shirts, pants, hats, and sunglasses.
- children under 6 months of age: Ask a doctor.

Other Information

- protect the product in this container from excessive heat and direct sun.

Inactive ingredients

Water (Aqua/Eau), Aloe Barbadensis Leaf Juice (Aloe Vera Gel from Aruba), VP/Eicosene Copolymer, Cetearyl Alcohol, Ceteth-20 Phosphate, Dimethicone, Tocopheryl Acetate (Vitamin E Acetate), Simmondsia Chinensis (Jojoba) Seed Oil, Cocos Nucifera (Coconut) Oil, Caprylyl Glycol, Myristyl Laurate, Glyceryl Laurate, Myristyl Myristate, Fragrance (Parfum), Glyceryl Undecylenate, Carbomer, Aminomethyl Propanol.